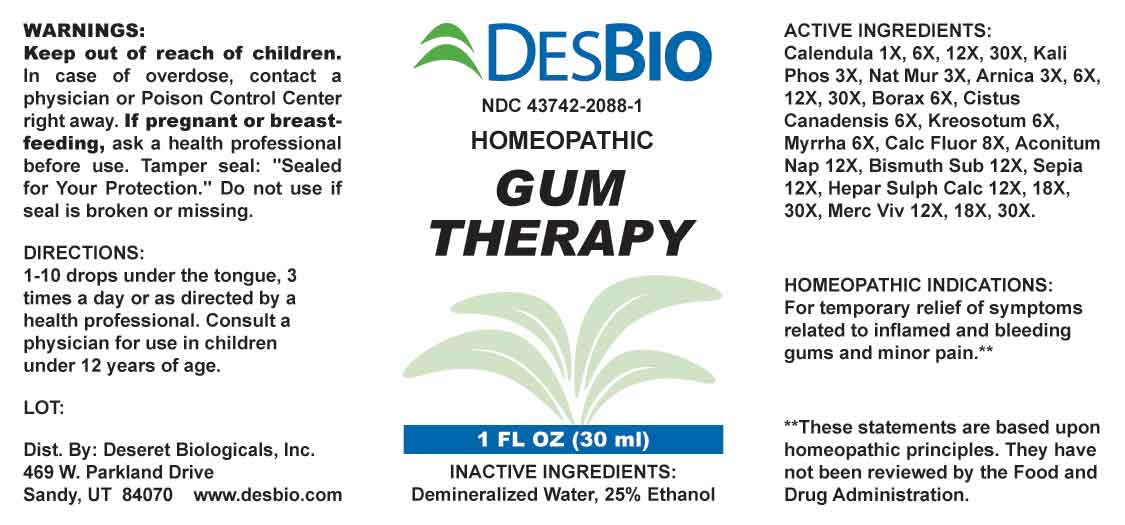 DRUG LABEL: Gum Therapy
NDC: 43742-2088 | Form: LIQUID
Manufacturer: Deseret Biologicals
Category: homeopathic | Type: HUMAN OTC DRUG LABEL
Date: 20240828

ACTIVE INGREDIENTS: CALENDULA OFFICINALIS FLOWERING TOP 1 [hp_X]/1 mL; DIBASIC POTASSIUM PHOSPHATE 3 [hp_X]/1 mL; SODIUM CHLORIDE 3 [hp_X]/1 mL; ARNICA MONTANA WHOLE 3 [hp_X]/1 mL; SODIUM BORATE 6 [hp_X]/1 mL; HELIANTHEMUM CANADENSE 6 [hp_X]/1 mL; WOOD CREOSOTE 6 [hp_X]/1 mL; MYRRH 6 [hp_X]/1 mL; CALCIUM FLUORIDE 8 [hp_X]/1 mL; ACONITUM NAPELLUS WHOLE 12 [hp_X]/1 mL; BISMUTH SUBNITRATE 12 [hp_X]/1 mL; SEPIA OFFICINALIS JUICE 12 [hp_X]/1 mL; CALCIUM SULFIDE 12 [hp_X]/1 mL; MERCURY 12 [hp_X]/1 mL
INACTIVE INGREDIENTS: WATER; ALCOHOL

DRUG FACTS:

ACTIVE INGREDIENTS:

Calendula Officinalis 1X, 6X, 12X, 30X, Kali Phosphoricum 3X, Natrum Muriaticum 3X, Arnica Montana 3X, 6X, 12X, 30X, Borax 6X, Cistus Canadensis 6X, Kreosotum 6X, Myrrha 6X, Calcarea Fluorica 8X, Aconitum Napellus 12X, Bismuthum Subnitricum 12X, Sepia 12X, Hepar Sulphuris Calcareum 12X, 18X, 30X, Mercurius Vivus 12X, 18X, 30X.

PURPOSE:

For temporary relief of symptoms related to inflamed and bleeding gums and minor pain.**

**These statements are based upon homeopathic principles. They have not been reviewed by the Food and Drug Administration.

WARNINGS:

Keep out of reach of children. In case of overdose, contact a physician or Poison Control Center right away.

If pregnant or breast-feeding, ask a health professional before use.

Tamper seal: "Sealed for Your Protection." Do not use if seal is broken or missing.

KEEP OUT OF REACH OF CHILDREN:

In case of overdose, contact physician or Poison Control Center right away.

DIRECTIONS:

1-10 drops under the tongue, 3 times a day or as directed by a health professional. Consult a physician for use in children under 12 years of age.

INDICATIONS:

For temporary relief of symptoms related to inflamed and bleeding gums and minor pain.**

**These statements are based upon homeopathic principles. They have not been reviewed by the Food and Drug Administration.

INACTIVE INGREDIENTS:

Demineralized Water, 25% Ethanol

QUESTIONS:

Dist. By: Deseret Biologicals, Inc.

469 W. Parkland Drive

Sandy, UT 84070 www.desbio.com

PACKAGE LABEL DISPLAY:

DESBIO
NDC 43742-2088-1
HOMEOPATHIC
GUM
THERAPY
1 FL OZ (30 ml)